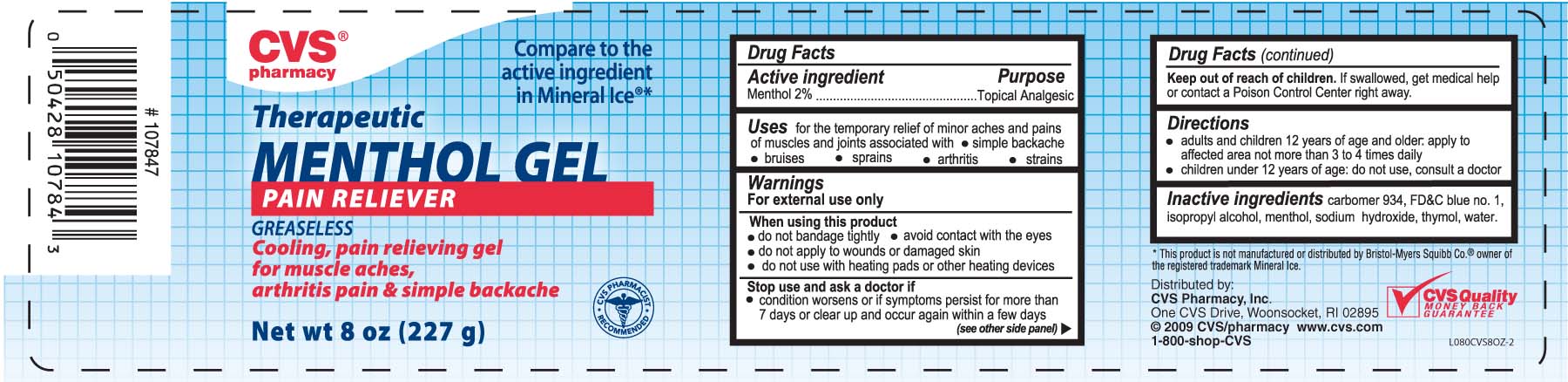 DRUG LABEL: CVS Therapeutic Menthol Pain Reliever
NDC: 59779-056 | Form: GEL
Manufacturer: CVS Pharmacy
Category: otc | Type: HUMAN OTC DRUG LABEL
Date: 20100710

ACTIVE INGREDIENTS: MENTHOL 20 mg/1 g
INACTIVE INGREDIENTS: ISOPROPYL ALCOHOL; CARBOMER 934; WATER; THYMOL; FD&C BLUE NO. 1; SODIUM HYDROXIDE

DRUG FACTS

Active ingredient Purpose
Menthol 2%...................................................Topical Analgesic

PURPOSE

Uses for the temporary relief of minor aches and pains of muscles and joints
associated with - simple backache - bruises - sprains - arthritis - strains

Keep out of reach of children. If swallowed, get medical help or contact a
Poison Control Center right away.

INDICATIONS AND USAGE

Uses for the temporary relief of minor aches and pains of muscles and joints
associated with - simple backache - bruises - sprains - arthritis - strains

Warnings
For external use only
When using this product
- do not bandage tightly - avoid contact with the eyes
- do not apply to wounds or damaged skin
- do not use with heating pads or other heating devices
Stop use and ask a doctor if - condition worsens or if symptoms persist
for more than 7 days or clear up and occur again within a few days
Keep out of reach of children.If swallowed, get medical help or contact a
Poison Control Center right away.

Directions
- adults and children 12 years of age and older, apply to affected area not more than 3 to 4 times daily
- children under 12 years of age: do not use, consult a doctor

Inactive Ingredients
carbomer 934, FDandC blue no. 1, isopropyl alcohol, menthol, sodium hydroxide, thymol, water